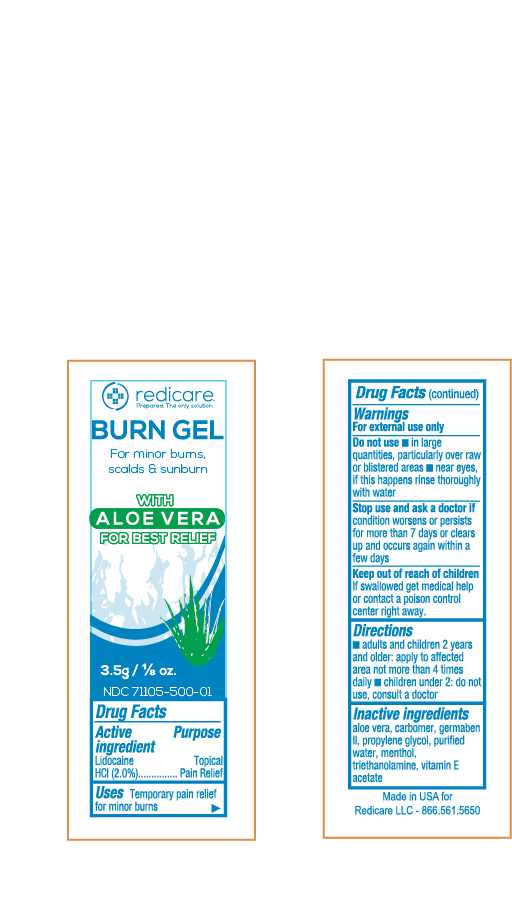 DRUG LABEL: Redicare Burn Gel
NDC: 71105-500 | Form: GEL
Manufacturer: Redicare LLC
Category: otc | Type: HUMAN OTC DRUG LABEL
Date: 20250305

ACTIVE INGREDIENTS: LIDOCAINE HYDROCHLORIDE 20 mg/1 g
INACTIVE INGREDIENTS: DIAZOLIDINYL UREA; WATER; PROPYLENE GLYCOL; MENTHOL; ALPHA-TOCOPHEROL ACETATE; TROLAMINE; ALOE VERA LEAF

Burn Gel USA

Active Ingredient

Lidocaine HCl 2.0%

Purpose

Topical pain relief

Uses

Temporary pain relief for minor burns

Warnings

For external use only

Do not use

- In large quantities, particularly over raw or blistered areas
- near eyes, if this happens rinse thoroughly with water.

Stop use and ask doctor

if condition worsens or persists for more than 7 days or clears up and occurs again within a few days

Keep out of reach of children.

If swallowed get medical help or contact a Poison Control Center right away

Directions

- for adults and children 2 years and older: apply to affected area not more than 4 times daily
- children under 2: do not use, consult a doctor

Inactive Ingredients

- aloe vera
- carbomer
- germaben II
- propylene glycol
- purified water
- menthol
- triethanolamine
- vitamin E acetate

PACKAGE LABEL

REDICARE

BURN GEL

for minor burns, scalds & sunburn

WITH ALOE VERA FOR BEST RELIEF

3.5g / 1/8 oz.

NDC 71105-500-01

DRUG FACTS...